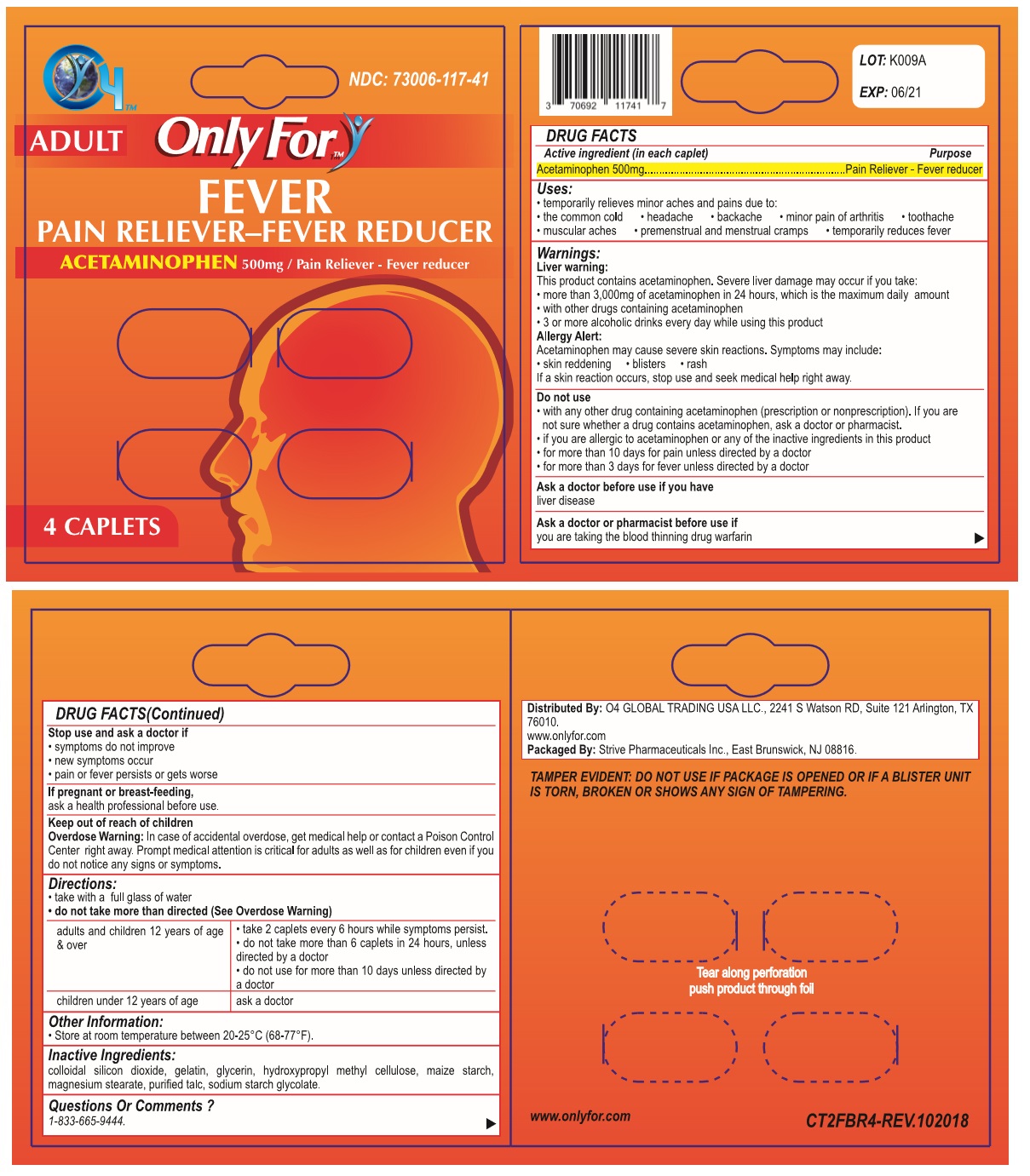 DRUG LABEL: Only For
NDC: 73006-117 | Form: TABLET
Manufacturer: O4 Global Trading Usa, Llc 
Category: otc | Type: HUMAN OTC DRUG LABEL
Date: 20190509

ACTIVE INGREDIENTS: ACETAMINOPHEN 500 mg/1 1
INACTIVE INGREDIENTS: SILICON DIOXIDE; GELATIN, UNSPECIFIED; GLYCERIN; HYPROMELLOSE 2910 (5 MPA.S); STARCH, CORN; MAGNESIUM PALMITOSTEARATE; TALC; SODIUM STARCH GLYCOLATE TYPE A POTATO

Only For- FEVER

Active ingredient (in each caplet)

Acetaminophen 500mg

Purpose

Pain Reliever - Fever reducer

Uses:

• temporarily relieves minor aches and pains due to:
• the common cold • headache • backache • minor pain of arthritis • toothache • muscular aches • premenstrual and menstrual cramps • temporarily reduces fever

Warnings:

Liver warning:
This product contains acetaminophen. Severe liver damage may occur if you take:
• more than 3,000mg of acetaminophen in 24 hours, which is the maximum daily amount
• with other drugs containing acetaminophen
• 3 or more alcoholic drinks every day while using this product

Allergy alert:
Acetaminophen may cause severe skin reactions. Symptoms may include:
• skin reddening • blisters • rash
If a skin reaction occurs, stop use and seek medical help right away.

Do not use
• with any other drug containing acetaminophen (prescription or nonprescription). If you are not sure whether a drug contains acetaminophen, ask a doctor or pharmacist.
• if you are allergic to acetaminophen or any of the inactive ingredients in this product
• for more than 10 days for pain unless directed by a doctor
• for more than 3 days for fever unless directed by a doctor

Ask a doctor before use if you have
liver disease

Ask a doctor or a pharmacist before use if
you are taking the blood thinning drug warfarin

Stop use and ask a doctor if
• symptoms do not improve
• new symptoms occur
• pain or fever persists or gets worse

If pregnant or breast-feeding,
ask a health professional before use.

Keep out of reach of children

Overdose Warning: In case of accidental overdose, get medical help or contact a Poison Control Center right away. Prompt medical attention is critical for adults as well as for children even if you do not notice any signs or symptoms.

Directions:

- take with a full glass of water
- do not take more than directed (See Overdose Warning)

adults and children 12 years of age & over | • take 2 caplets every 6 hours while symptoms persist.; • do not take more than 6 caplets in 24 hours, unless directed by a doctor; • do not use for more than 10 days unless directed by a doctor
children under 12 years of age | ask a doctor

Other Information:

• Store at room temperature between 20-25°C (68-77°F).

Inactive Ingredients:

colloidal silicon dioxide, gelatin, glycerin, hydroxypropyl methyl cellulose, maize starch, magnesium stearate, purified talc, sodium starch glycolate.

Questions Or Comments ?

1-833-665-9444.

NDC: 73006-117-41

ADULT

PAIN RELIEVER-FEVER REDUCER

Distributed By: O4 GLOBAL TRADING USA LLC., 2241 S Watson RD, Suite 121 Arlington, TX 76010.
www.onlyfor.com
Packaged By: Strive Pharmaceuticals Inc., East Brunswick, NJ 08816.

TAMPER EVIDENT: DO NOT USE IF PACKAGE IS OPENED OR IF A BLISTER UNIT IS TORN, BROKEN OR SHOWS ANY SIGN OF TAMPERING.

Tear along perforation push product through foil